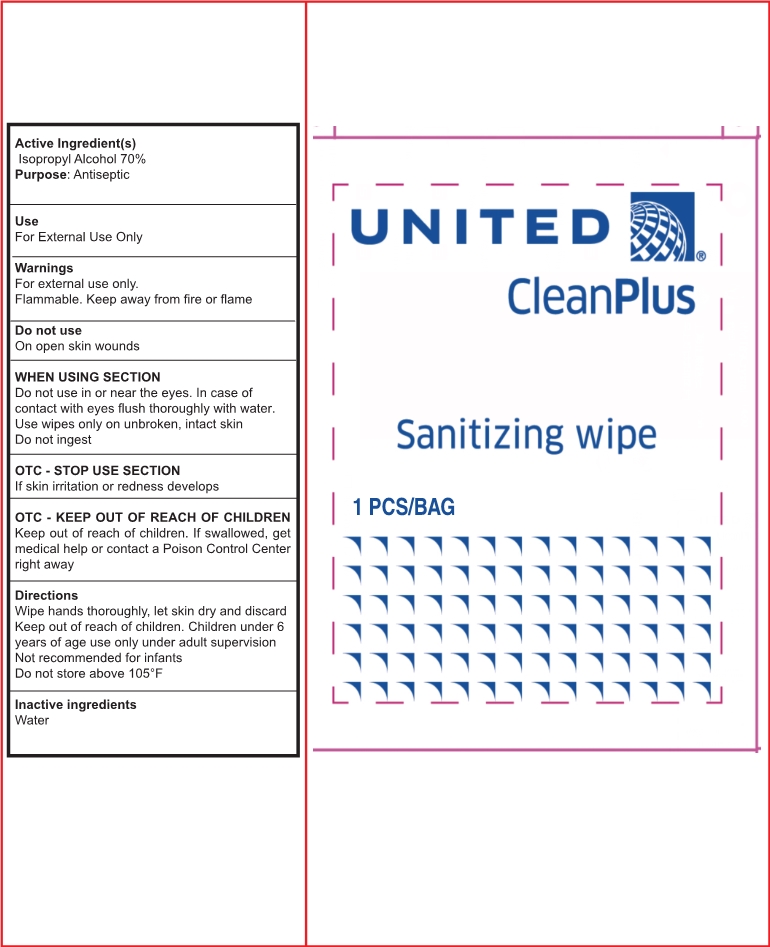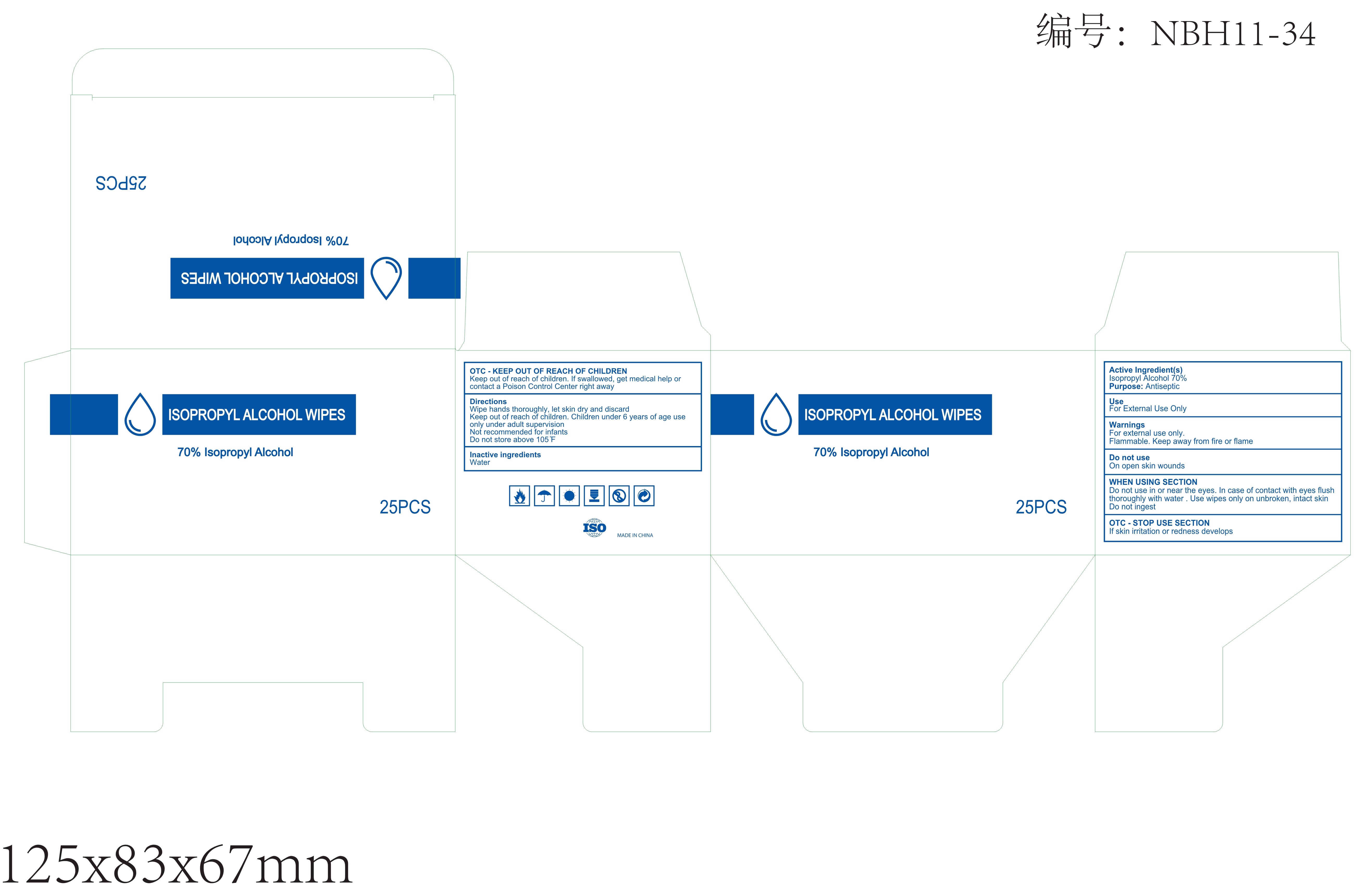 DRUG LABEL: SANITIZING WIPE
NDC: 72766-004 | Form: CLOTH
Manufacturer: Yangzhou Suxiang Medical Instrument Co., Ltd.
Category: otc | Type: HUMAN OTC DRUG LABEL
Date: 20200821

ACTIVE INGREDIENTS: ISOPROPYL ALCOHOL 70 mL/100 1
INACTIVE INGREDIENTS: WATER

72766-004
SANITIZING WIPE

Active Ingredient(s)

Isopropyl Alcohol 70%

Purpose

Antiseptic

Use

For External Use Only

Warnings

For external use only.
Flammable. Keep away from fire or flame

Do not use

On open skin wounds

Do not use in or near the eyes. In case of contact with eyes flush thoroughly with water.
Use wipes only on unbroken, intact skin
Do not ingest

STOP USE

If skin irritation or redness develops

Keep out of reach of children. If swallowed, get medical help or contact a Poison Control Center right away

Directions

Wipe hands thoroughly, let skin dry and discard
Keep out of reach of children. Children under 6 years of age use only under adult supervision
Not recommended for infants
Do not store above 105°F

Other information

/

Inactive ingredients

Water